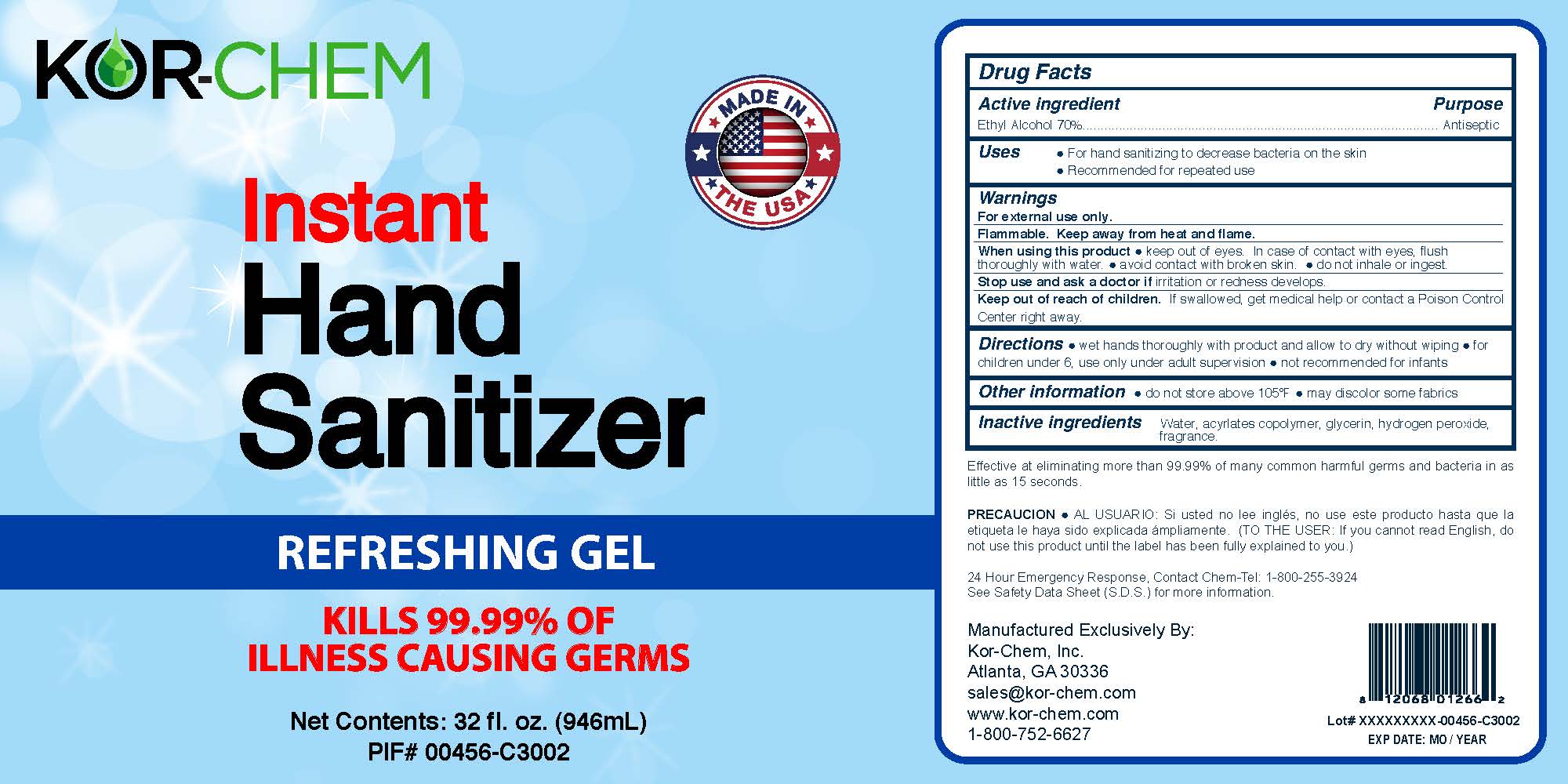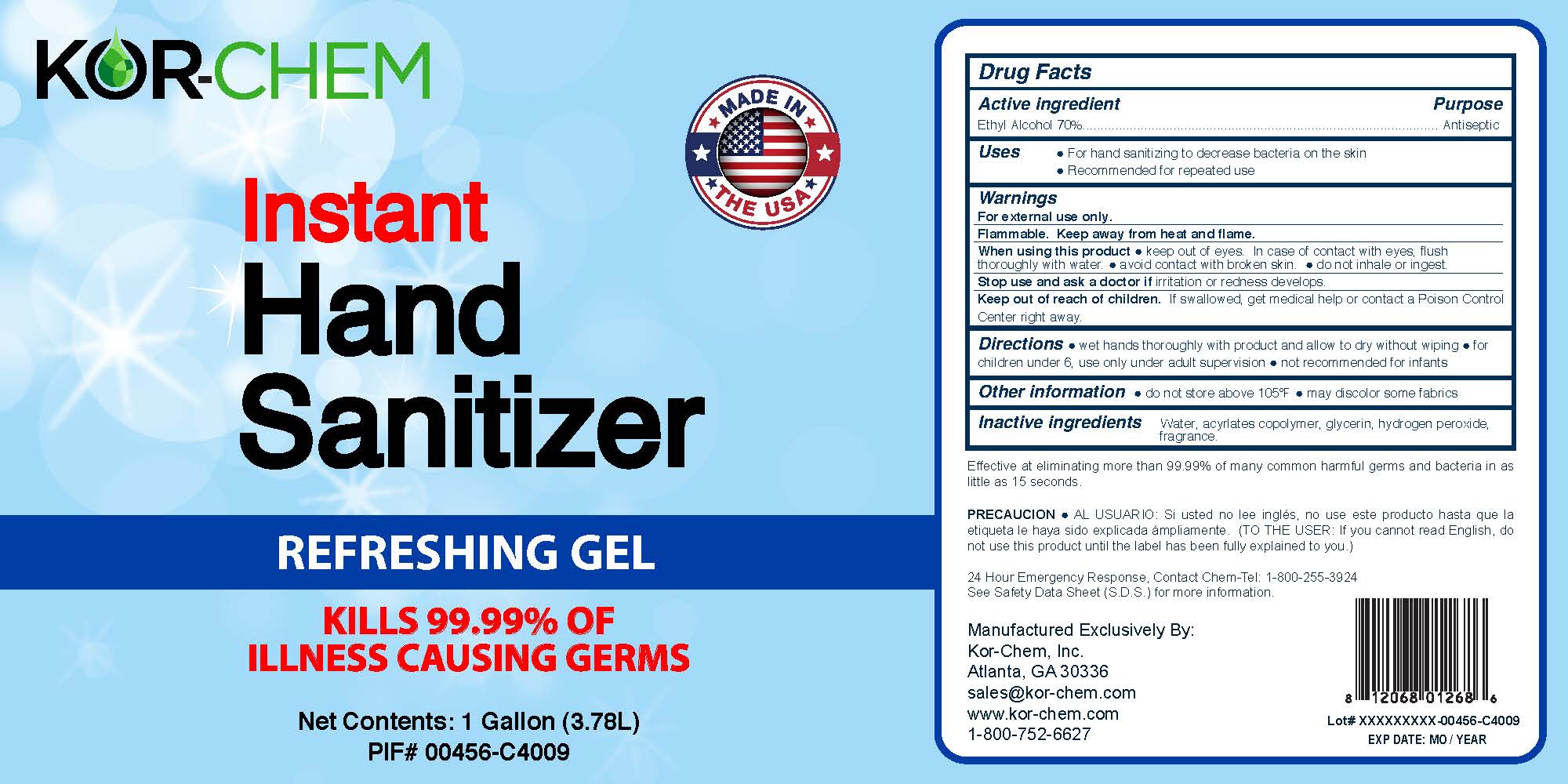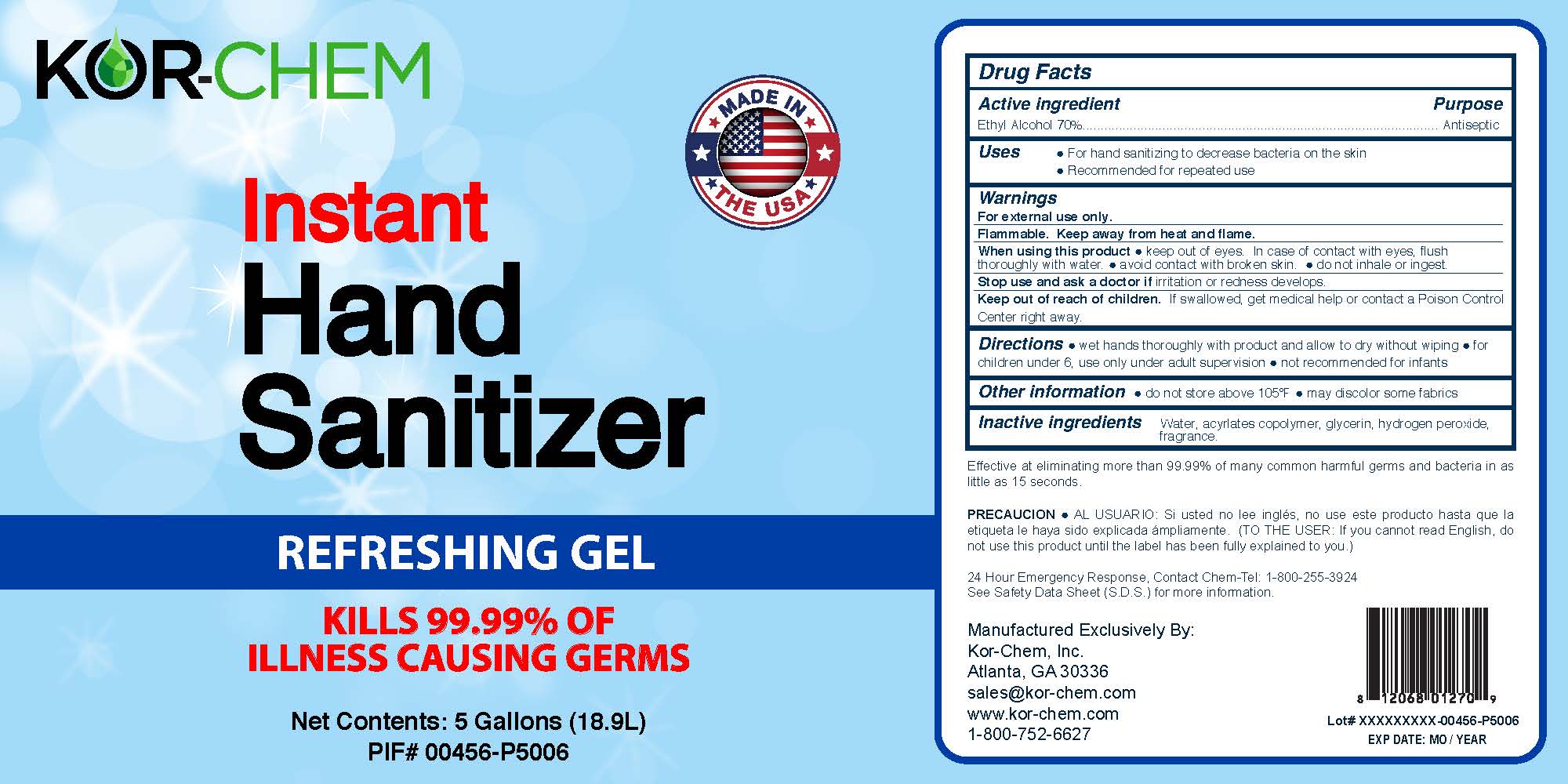 DRUG LABEL: Instant Hand Sanitizer
NDC: 62881-001 | Form: GEL
Manufacturer: Kor-Chem, Inc.
Category: otc | Type: HUMAN OTC DRUG LABEL
Date: 20220131

ACTIVE INGREDIENTS: ALCOHOL 75 L/100 L
INACTIVE INGREDIENTS: WATER 17.82 L/100 L; GLYCERIN 0.725 L/100 L; ACRYLIC ACID/SODIUM ACRYLATE COPOLYMER (1:1; 600 MPA.S AT 0.2%) 6 L/100 L; HYDROGEN PEROXIDE 0.125 L/100 L

Active ingredient Purpose
Ethyl Alcohol 70%.................................................................................................. Antiseptic

INACTIVE INGREDIENT

Water, acyrlates copolymer, glycerin, hydrogen peroxide, fragrance.

WARNINGS

For external use only.
Flammable. Keep away from heat and flame.
When using this product ● keep out of eyes. In case of contact with eyes, flush thoroughly with water. ● avoid contact with broken skin. ● do not inhale or ingest.
Stop use and ask a doctor if irritation or redness develops.
Keep out of reach of children. If swallowed, get medical help or contact a Poison Control Center right away.

OTHER SAFETY INFORMATION

do not store above 105°F ● may discolor some fabrics

INDICATIONS AND USAGE

Uses ● For hand sanitizing to decrease bacteria on the skin
● Recommended for repeated use

DOSAGE AND ADMINISTRATION

Directions ● wet hands thoroughly with product and allow to dry without wiping ● for children under 6, use only under adult supervision ● not recommended for infants

Keep out of reach of children. If swallowed, get medical help or contact a Poison Control Center right away.